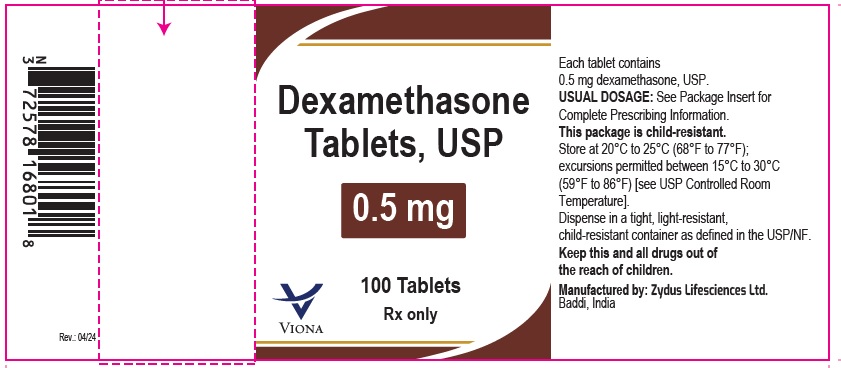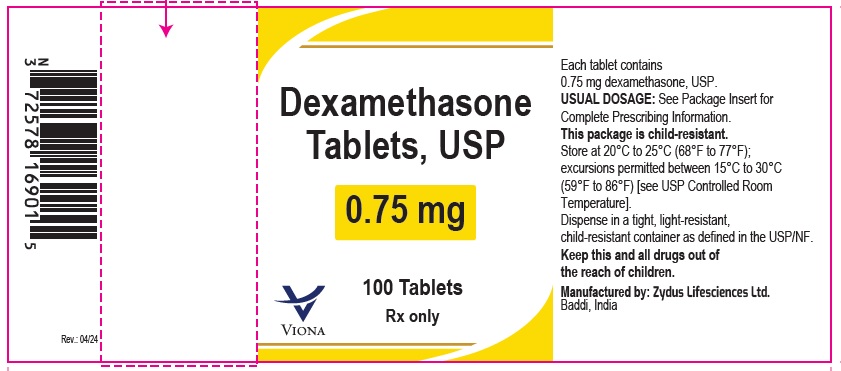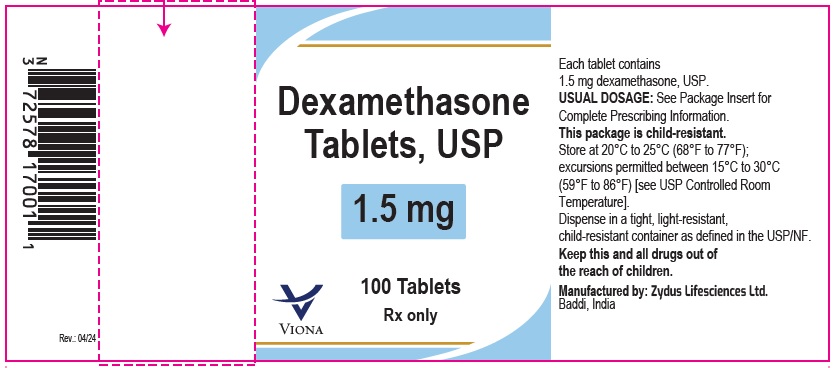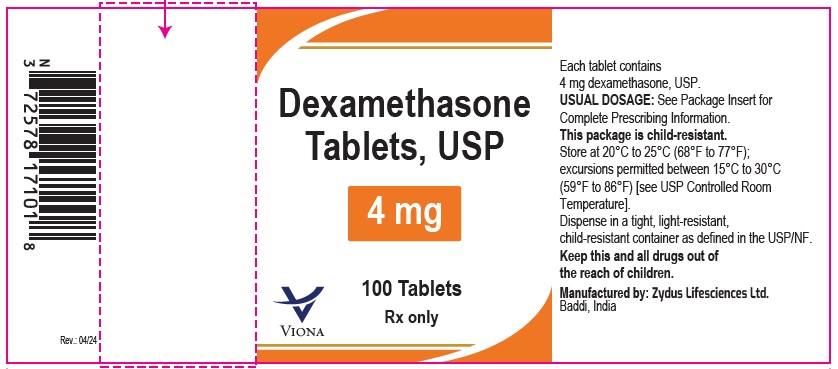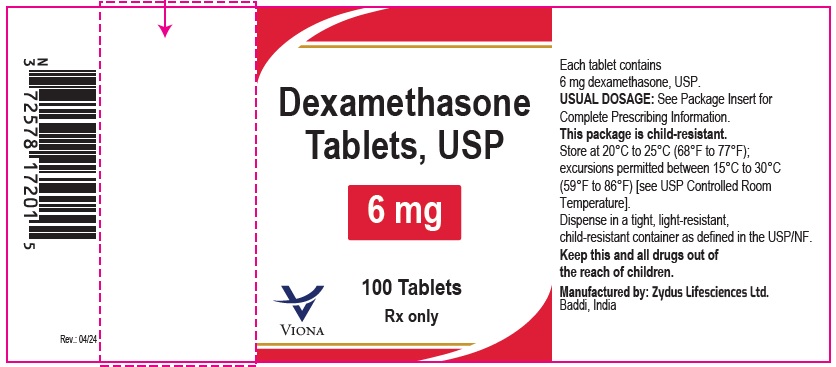 DRUG LABEL: Dexamethasone
NDC: 70771-1699 | Form: TABLET
Manufacturer: Zydus Lifesciences Limited
Category: prescription | Type: HUMAN PRESCRIPTION DRUG LABEL
Date: 20240330

ACTIVE INGREDIENTS: DEXAMETHASONE 4 mg/1 1
INACTIVE INGREDIENTS: FD&C BLUE NO. 1 ALUMINUM LAKE; FERRIC OXIDE YELLOW; LACTOSE MONOHYDRATE; MAGNESIUM STEARATE; STARCH, CORN; SUCROSE

Dexamethasone Tablets

PACKAGE LABEL.PRINCIPAL DISPLAY PANEL

NDC 70771-1704-1

Dexamethasone Tablets, USP 0.5 mg

100 Tablets

Rx only

Zydus

NDC 70771-1705-1

Dexamethasone Tablets, USP 0.75 mg

100 Tablets

Rx only

Zydus

NDC 70771-1707-1

Dexamethasone Tablets, USP 1.5 mg

100 Tablets

Rx only

Zydus

NDC 70771-1699-1

Dexamethasone Tablets, USP 4 mg

100 Tablets

Rx only

Zydus

NDC 70771-1700-1

Dexamethasone Tablets, USP 6 mg

100 Tablets

Rx only

Zydus